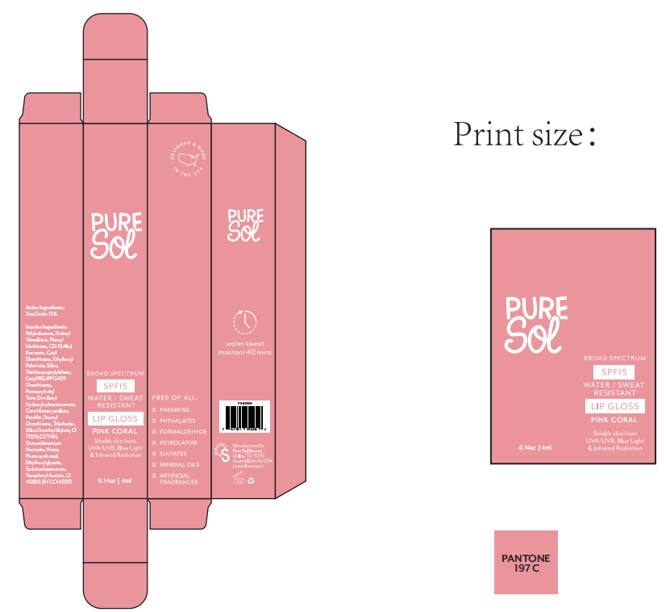 DRUG LABEL: PURE SOL  SPF15  Lip Gloss Pink coral
NDC: 84090-008 | Form: LIQUID
Manufacturer: Brand 2022b LLC
Category: otc | Type: HUMAN OTC DRUG LABEL
Date: 20251004

ACTIVE INGREDIENTS: ZINC OXIDE 7.2 g/100 mL
INACTIVE INGREDIENTS: ALPHA-TOCOPHEROL ACETATE; HYDROGENATED POLYISOBUTENE 8; PHENYL METHICONE (500 CST); CETYL PEG/PPG-10/1 DIMETHICONE (HLB 2); TRIBEHENIN; CI 77491; WATER; ETHYLHEXYLGLYCERIN; MICROCRYSTALLINE WAX; FLAVOR SPICE MINT N&A110589; TRIDECYL TRIMELLITATE; CI 45380; SILICA; CETYL DIMETHICONE/BIS-VINYLDIMETHICONE CROSSPOLYMER; ETHYLHEXYL PALMITATE; STEARYL TRISILOXANE; TRIETHOXYCAPRYLYLSILANE; PENTAERYTHRITYL TETRA-DI-T-BUTYL HYDROXYHYDROCINNAMATE; PARAFFIN; SORBITAN ISOSTEARATE; C12-15 ALKYL BENZOATE; SILICA DIMETHYL SILYLATE; MICA; CI 45370; DISTEARDIMONIUM HECTORITE; BHT; PHENOXYETHANOL

84090-008-01. PURE SOL SPF15 Lip Gloss(Pink coral) —liquid-4ml

ACTIVE INGREDIENT

Zinc Oxide 7.20%

PURPOSE

Helps prevent sunburn.

Keep out of reach of children.

If swallowed, get medical help or contact a Poison Control Center right away.

WARNINGS

For external use only

When using this product keep out of eyes.

Rinse with water to remove - do not use on broken skin.

DOSAGE AND ADMINISTRATION

■Apply liberally and evenly 15 minutes before sun exposure.

■Reapply at least every two hours.

■Sun Protection Measures: Spending time in the sun increases

INDICATIONS AND USAGE

your risk of skin cancer and early skin aging. To decrease this risk,

regularly use a sunscreen with a Broad Spectrum SPF value of 15

or higher and other sun protection measures including:

• limit time in the sun, especially from 10 AM – 2 PM

• wear long sleeve shirts, pants, hats, and sunglasse

INACTIVE INGREDIENT

POLYISOBUTENE
TRIDECYL TRIMELLITATE
PHENYL METHICONE
C12-15 ALKYL BENZOATE
CETYL DIMETHICONE
ETHYLHEXYL PALMITATE
SILICA
TRIETHOXYCAPRYLYLSILANE
CETYL PEG/PPG-10/1 DIMETHICONE
PENTAERYTHRITYL TETRA-DI-t-BUTYL HYDROXYHYDROCINNAMATE
CERA MICROCRISTALLINA
PARAFFIN
STEARYL DIMETHICONE
TRIBEHENIN
CERA MICROCRISTALLINA
FLAVOR
SILICA DIMETHYL SILYLATE
CI 77019
CI 77491
DISTEARDIMONIUM HECTORITE
WATER
PHENOXYETHANOL
ETHYLHEXYLGLYCERIN
SORBITAN ISOSTEARATE
TOCOPHERYL ACETATE
CI 45380
BHT
CI 45370